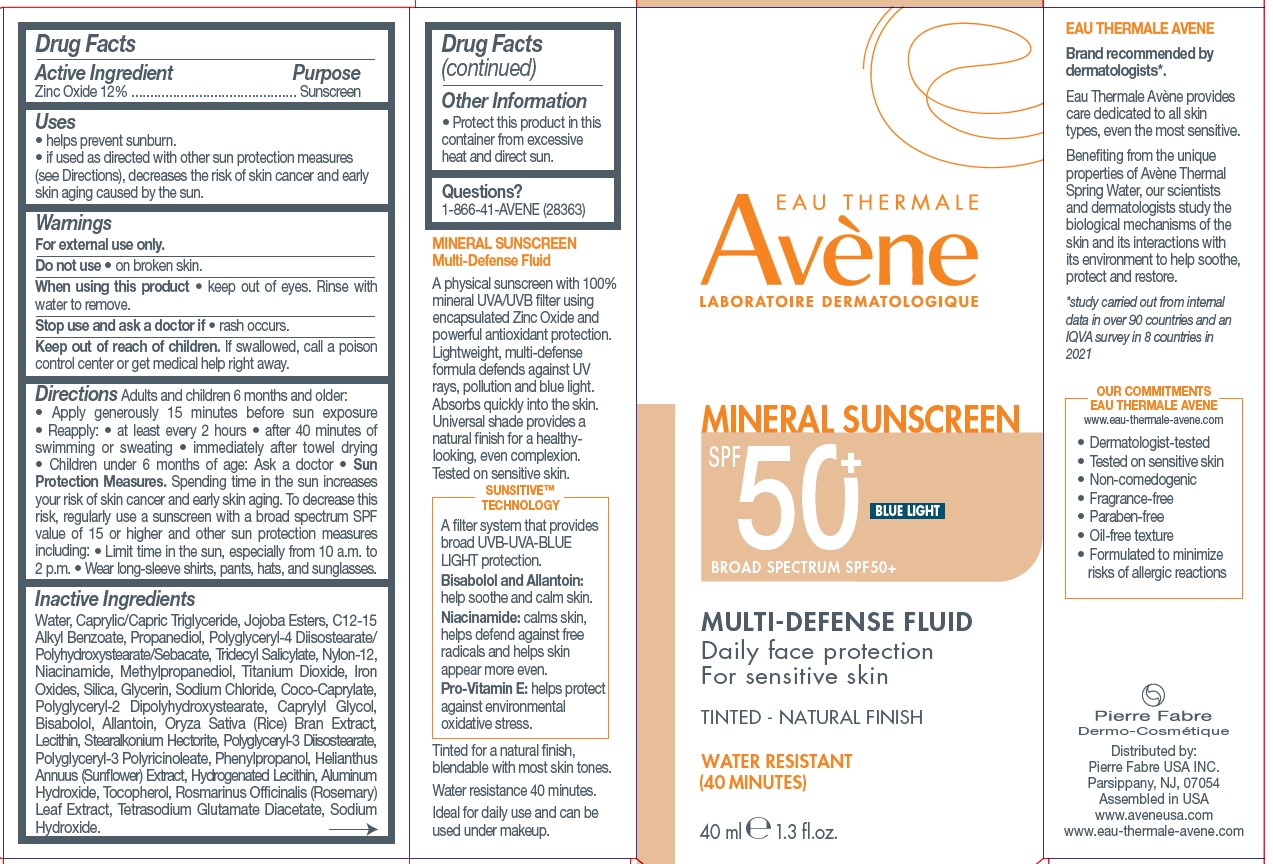 DRUG LABEL: Avene Multi-Defense Fluid Tinted
NDC: 64760-779 | Form: LOTION
Manufacturer: Pierre Fabre USA Inc.
Category: otc | Type: HUMAN OTC DRUG LABEL
Date: 20240308

ACTIVE INGREDIENTS: ZINC OXIDE 120 mg/1 mL
INACTIVE INGREDIENTS: POLYGLYCERYL-4 DIISOSTEARATE/POLYHYDROXYSTEARATE/SEBACATE; NYLON-12; MEDIUM-CHAIN TRIGLYCERIDES; SILICON DIOXIDE; COCO-CAPRYLATE; POLYGLYCERYL-2 DIPOLYHYDROXYSTEARATE; ALLANTOIN; HYDROGENATED SOYBEAN LECITHIN; ALUMINUM HYDROXIDE; TOCOPHEROL; ROSEMARY; STEARALKONIUM HECTORITE; PHENYLPROPANOL; TETRASODIUM GLUTAMATE DIACETATE; WATER; PROPANEDIOL; TRIDECYL SALICYLATE; JOJOBA OIL, RANDOMIZED; ALKYL (C12-15) BENZOATE; NIACINAMIDE; TITANIUM DIOXIDE; FERRIC OXIDE RED; GLYCERIN; SODIUM CHLORIDE; LECITHIN, SOYBEAN; POLYGLYCERYL-3 DIISOSTEARATE; POLYGLYCERYL-3 PENTARICINOLEATE; HELIANTHUS ANNUUS FLOWERING TOP; SODIUM HYDROXIDE; LEVOMENOL; METHYLPROPANEDIOL; CAPRYLYL GLYCOL; RICE BRAN

Avene Multi-Defense Fluid Tinted

Active Ingredient

Zinc Oxide 12%

Purpose

Sunscreen

Uses

• helps prevent sunburn.

• if used as directed with other sun protection measures (see Directions), decreases the risk of skin cancer and early skin aging caused by the sun.

Warnings

For external use only.

Do not use

• on broken skin.

When using this product

• keep out of eyes. Rinse with water to remove.

Stop use and ask a doctor if

• rash occurs.

Keep out of reach of children.

If swallowed, call a poison control center or get medical help right away.

Directions

Adults and children 6 months and older:

• Apply generously 15 minutes before sun exposure • Reapply: • at least every 2 hours • after 40 minutes of swimming or sweating • immediately after towel drying • Children under 6 months of age: Ask a doctor • Sun Protection Measures. Spending time in the sun increases your risk of skin cancer and early skin aging. To decrease this risk, regularly use a sunscreen with a broad spectrum SPF value of 15 or higher and other sun protection measures including: • Limit time in the sun, especially from 10 a.m. to 2 p.m. • Wear long-sleeve shirts, pants, hats, and sunglasses.

Inactive Ingredients

Water, Caprylic/Capric Triglyceride, Jojoba Esters, C12-15 Alkyl Benzoate, Propanediol, Polyglyceryl-4 Diisostearate/Polyhydroxystearate/Sebacate, Tridecyl Salicylate, Nylon-12, Niacinamide, Methylpropanediol, Titanium Dioxide, Iron
Oxides, Silica, Glycerin, Sodium Chloride, Coco-Caprylate, Polyglyceryl-2 Dipolyhydroxystearate, Caprylyl Glycol, Bisabolol, Allantoin, Oryza Sativa (Rice) Bran Extract, Lecithin, Stearalkonium Hectorite, Polyglyceryl-3 Diisostearate, Polyglyceryl-3 Polyricinoleate, Phenylpropanol, Helianthus Annuus (Sunflower) Extract, Hydrogenated Lecithin, Aluminum Hydroxide, Tocopherol, Rosmarinus Officinalis (Rosemary) Leaf Extract, Tetrasodium Glutamate Diacetate, Sodium Hydroxide.

Other Information

• Protect this product in this container from excessive heat and direct sun.

Questions?

1-866-41-AVENE (28363)